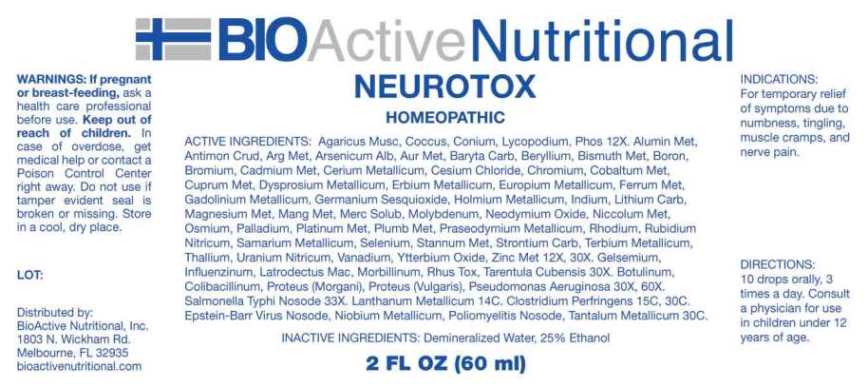 DRUG LABEL: Neurotox
NDC: 43857-0632 | Form: LIQUID
Manufacturer: BioActive Nutritional, Inc.
Category: homeopathic | Type: HUMAN OTC DRUG LABEL
Date: 20250519

ACTIVE INGREDIENTS: AMANITA MUSCARIA FRUITING BODY 12 [hp_X]/1 mL; PROTORTONIA CACTI 12 [hp_X]/1 mL; CONIUM MACULATUM FLOWERING TOP 12 [hp_X]/1 mL; LYCOPODIUM CLAVATUM SPORE 12 [hp_X]/1 mL; PHOSPHORUS 12 [hp_X]/1 mL; ALUMINUM 12 [hp_X]/1 mL; ANTIMONY TRISULFIDE 12 [hp_X]/1 mL; SILVER 12 [hp_X]/1 mL; ARSENIC TRIOXIDE 12 [hp_X]/1 mL; GOLD 12 [hp_X]/1 mL; BARIUM CARBONATE 12 [hp_X]/1 mL; BERYLLIUM 12 [hp_X]/1 mL; BISMUTH 12 [hp_X]/1 mL; BORON 12 [hp_X]/1 mL; BROMINE 12 [hp_X]/1 mL; CADMIUM 12 [hp_X]/1 mL; CERIUM 12 [hp_X]/1 mL; CESIUM CHLORIDE 12 [hp_X]/1 mL; CHROMIUM 12 [hp_X]/1 mL; COBALT 12 [hp_X]/1 mL; COPPER 12 [hp_X]/1 mL; DYSPROSIUM 12 [hp_X]/1 mL; ERBIUM 12 [hp_X]/1 mL; EUROPIUM 12 [hp_X]/1 mL; IRON 12 [hp_X]/1 mL; GADOLINIUM 12 [hp_X]/1 mL; GERMANIUM SESQUIOXIDE 12 [hp_X]/1 mL; HOLMIUM 12 [hp_X]/1 mL; INDIUM 12 [hp_X]/1 mL; LITHIUM CARBONATE 12 [hp_X]/1 mL; MAGNESIUM 12 [hp_X]/1 mL; MANGANESE 12 [hp_X]/1 mL; MERCURIUS SOLUBILIS 12 [hp_X]/1 mL; MOLYBDENUM 12 [hp_X]/1 mL; NEODYMIUM OXIDE 12 [hp_X]/1 mL; NICKEL 12 [hp_X]/1 mL; OSMIUM 12 [hp_X]/1 mL; PALLADIUM 12 [hp_X]/1 mL; PLATINUM 12 [hp_X]/1 mL; LEAD 12 [hp_X]/1 mL; PRASEODYMIUM 12 [hp_X]/1 mL; RHODIUM 12 [hp_X]/1 mL; RUBIDIUM NITRITE 12 [hp_X]/1 mL; SAMARIUM 12 [hp_X]/1 mL; SELENIUM 12 [hp_X]/1 mL; TIN 12 [hp_X]/1 mL; STRONTIUM CARBONATE 12 [hp_X]/1 mL; TERBIUM 12 [hp_X]/1 mL; THALLIUM 12 [hp_X]/1 mL; URANYL NITRATE HEXAHYDRATE 12 [hp_X]/1 mL; VANADIUM 12 [hp_X]/1 mL; YTTERBIUM OXIDE 12 [hp_X]/1 mL; ZINC 12 [hp_X]/1 mL; GELSEMIUM SEMPERVIRENS ROOT 30 [hp_X]/1 mL; INFLUENZA A VIRUS A/VICTORIA/2570/2019 IVR-215 (H1N1) ANTIGEN (UV, FORMALDEHYDE INACTIVATED) 30 [hp_X]/1 mL; INFLUENZA A VIRUS A/DARWIN/9/2021 IVR-228 (H3N2) ANTIGEN (UV, FORMALDEHYDE INACTIVATED) 30 [hp_X]/1 mL; INFLUENZA B VIRUS B/AUSTRIA/1359417/2021 BVR-26 ANTIGEN (UV, FORMALDEHYDE INACTIVATED) 30 [hp_X]/1 mL; INFLUENZA B VIRUS B/PHUKET/3073/2013 ANTIGEN (UV, FORMALDEHYDE INACTIVATED) 30 [hp_X]/1 mL; LATRODECTUS MACTANS 30 [hp_X]/1 mL; MEASLES VIRUS 30 [hp_X]/1 mL; TOXICODENDRON PUBESCENS LEAF 30 [hp_X]/1 mL; CITHARACANTHUS SPINICRUS 30 [hp_X]/1 mL; BOTULINUM TOXIN TYPE A 30 [hp_X]/1 mL; ESCHERICHIA COLI 30 [hp_X]/1 mL; PROTEUS VULGARIS 30 [hp_X]/1 mL; PSEUDOMONAS AERUGINOSA 30 [hp_X]/1 mL; PROTEUS MORGANII 30 [hp_X]/1 mL; SALMONELLA ENTERICA SUBSP. ENTERICA SEROVAR TYPHI 33 [hp_X]/1 mL; LANTHANUM 14 [hp_C]/1 mL; CLOSTRIDIUM PERFRINGENS 15 [hp_C]/1 mL; HUMAN HERPESVIRUS 4 30 [hp_C]/1 mL; NIOBIUM 30 [hp_C]/1 mL; POLIOVIRUS 30 [hp_C]/1 mL; TANTALUM 30 [hp_C]/1 mL
INACTIVE INGREDIENTS: WATER; ALCOHOL

DRUG FACTS:

ACTIVE INGREDIENTS:

Agaricus Muscarius 12X, Coccus Cacti 12X, Conium Maculatum 12X, Lycopodium Clavatum 12X, Phosphorus 12X, Aluminium Metallicum 12X, 30X, Antimonium Crudum 12X, 30X, Argentum Metallicum 12X, 30X, Arsenicum Album 12X, 30X, Aurum Metallicum 12X, 30X, Baryta Carbonica 12X, 30X, Beryllium Metallicum 12X, 30X, Bismuthum Metallicum 12X, 30X, Boron 12X, 30X, Bromium 12X, 30X, Cadmium Metallicum 12X, 30X, Cerium Metallicum 12X, 30X, Cesium Chloride 12X, 30X, Chromium 12X, 30X, Cobaltum Metallicum 12X, 30X, Cuprum Metallicum 12X, 30X, Dysprosium Metallicum 12X, 30X, Erbium Metallicum 12X, 30X, Europium Metallicum 12X, 30X, Ferrum Metallicum 12X, 30X, Gadolinium Metallicum 12X, 30X, Germanium Sesquioxide 12X, 30X, Holmium Metallicum 12X, 30X, Indium Metallicum 12X, 30X, Lithium Carbonicum 12X, 30X, Magnesium Metallicum 12X, 30X, Manganum Metallicum 12X, 30X, Mercurius Solubilis 12X, 30X, Molybdenum 12X, 30X, Neodymium Oxide 12X, 30X, Niccolum Metallicum 12X, 30X, Osmium Metallicum 12X, 30X, Palladium Metallicum 12X, 30X, Platinum Metallicum 12X, 30X, Plumbum Metallicum 12X, 30X, Praseodymium Metallicum 12X, 30X, Rhodium Metallicum 12X, 30X, Rubidium Nitricum 12X, 30X, Samarium Metallicum 12X, 30X, Selenium Metallicum 12X, 30X, Stannum Metallicum 12X, 30X, Strontium Carbonicum 12X, 30X, Terbium Metallicum 12X, 30X, Thallium Metallicum 12X, 30X, Uranium Nitricum 12X, 30X, Vanadium Metallicum 12X, 30X, Ytterbium Oxide 12X, 30X, Zincum Metallicum 12X, 30X, Gelsemium Sempervirens 30X, Influenzinum 30X, Latrodectus Mactans 30X, Morbillinum 30X, Rhus Tox 30X, Tarentula Cubensis 30X, Botulinum 30X, 60X, Escherichia Coli Colibacillinum Cum Natrum Muriaticum 30X, 60X, Proteus (Vulgaris) 30X, 60X, Pseudomonas Aeruginosa 30X, 60X, Proteus (Morgani) 30X, 60X, Salmonella Typhi Nosode 33X, Lanthanum Metallicum 14C, Clostridium Perfringens 15C, 30C, Epstein-Barr Virus Nosode 30C, Niobium Metallicum 30C, Poliomyelitis Nosode 30C, Tantalum Metallicum 30C.

PURPOSE:

For temporary relief of symptoms due to numbness, tingling, muscle cramps, and nerve pain.

WARNINGS:

If pregnant or breast-feeding, ask a health care professional before use.

Keep out of reach of children. In case of overdose, get medical help or contact a Poison Control Center right away.

Do not use if tamper evident seal is broken or missing.

Store in cool, dry place.

KEEP OUT OF REACH OF CHILDREN:

In case of overdose, get medical help or contact a Poison Control Center right away.

DIRECTIONS:

10 drops orally, 3 times a day. Consult a physician for use in children under 12 years of age.

INDICATIONS:

For temporary relief of symptoms due to numbness, tingling, muscle cramps, and nerve pain.

INACTIVE INGREDIENTS:

Demineralized Water, 25% Ethanol

QUESTIONS:

Distributed by:
BioActive Nutritional, Inc.
1803 N. Wickham Rd.
Melbourne, FL 32935
bioactivenutritional.com

PACKAGE LABEL DISPLAY:

BIOActiveNutritional
NEUROTOX
HOMEOPATHIC
2 FL OZ (60 ml)